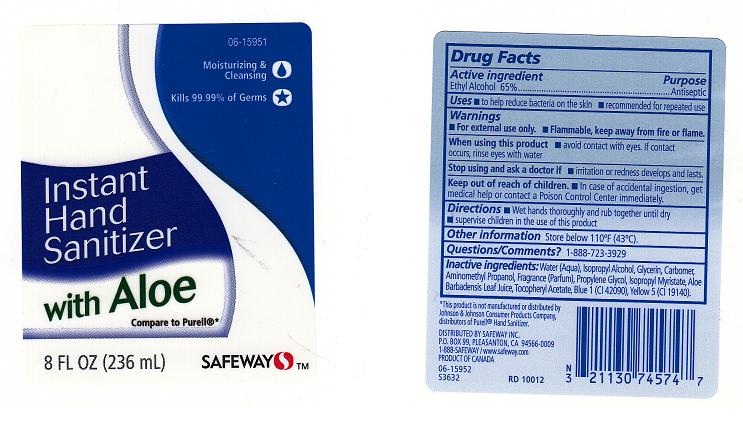 DRUG LABEL: SAFEWAY
NDC: 21130-255 | Form: LIQUID
Manufacturer: SAFEWAY INC
Category: otc | Type: HUMAN OTC DRUG LABEL
Date: 20111212

ACTIVE INGREDIENTS: ALCOHOL 65 mL/100 mL
INACTIVE INGREDIENTS: WATER; ISOPROPYL ALCOHOL; GLYCERIN; CARBOMER 934; AMINOMETHYLPROPANOL; PROPANEDIOL; ISOPROPYL MYRISTATE; ALOE VERA LEAF; TOCOPHEROL; FD&C BLUE NO. 1; FD&C YELLOW NO. 5

DRUG FACTS

ACTIVE INGREDIENT

ETHYL ALCOHOL 65%

PURPOSE

ANTISEPTIC

USES

TO HELP REDUCE BACTERIA ON THE SKIN. RECOMMENDED FOR REPEATED USE

WARNINGS

FOR EXTERNAL USE ONLY. FLAMMABLE, KEEP AWAY FROM FIRE OR FLAME

WHEN USING THIS PRODUCT

AVOID CONTACT WITH EYES. IF CONTACT OCCURS, RINSE EYES WITH WATER.

STOP USING AND ASK A DOCTOR IF

IRRITATION OR REDNESS DEVELOPS AND LASTS

KEEP OUT OF REACH OF CHILDREN.

IN CASE OF ACCIDENTAL INGESTION, GET MEDICAL HELP OR CONTACT A POISON CONTROL CENTER IMMEDIATELY

DIRECTIONS

WET HANDS THOROUGHLY AND RUB TOGETHER UNTIL DRY. SUPERVISE CHILDREN IN THE USE OF THIS PRODUCT.

QUESTIONS / COMMENTS

1-888-723-3929

OTHER INFORMATION

STORE BELOW 110 F (43 C)

INACTIVE INGREDIENTS

WATER (AQUA), ISOPROPYL ALCOHOL, GLYCERIN, CARBOMER, AMINOMETHYL PROPANOL, FRAGRANCE (PARFUM), PROPYLENE GLYCOL, ISOPROPYL MYRISTATE, ALOE BARBADENSIS LEAF JUICE, TOCOPHERYL ACETATE, BLUE 1 (CI 42090), YELLOW 5 (CI 19140).